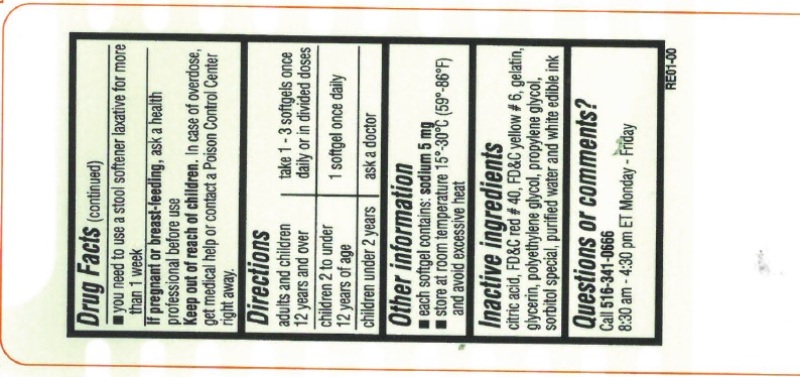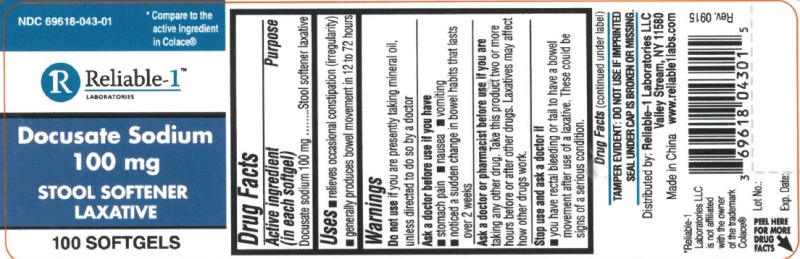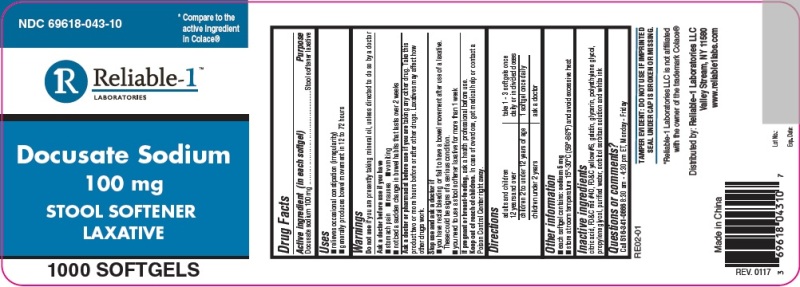 DRUG LABEL: Docusate Sodium
NDC: 69618-043 | Form: CAPSULE
Manufacturer: Reliable 1 Laboratories LLC
Category: otc | Type: HUMAN OTC DRUG LABEL
Date: 20191125

ACTIVE INGREDIENTS: DOCUSATE SODIUM 100 mg/1 1
INACTIVE INGREDIENTS: D&C RED NO. 33; ANHYDROUS CITRIC ACID; FD&C RED NO. 40; FD&C BLUE NO. 1; FD&C YELLOW NO. 6; WATER; SORBITOL; GELATIN; GLYCERIN; POLYETHYLENE GLYCOL, UNSPECIFIED; PROPYLENE GLYCOL

Docusate Sodium 100 mg

Drug Facts

Active ingredient (in each softgel)

Docusate sodium 100 mg

Purpose

Stool softener laxative

Uses

- relieves occasional constipation (irregularity)
- generally produces bowel movement in 12 to 72 hours

Warnings

Do not use if you are presently taking mineral oil, unless directed to do so by a doctor

Ask a doctor before use if you have

- stomach pain
- nausea
- vomiting
- noticed a sudden change in bowel habits that lasts over 2 weeks

Ask a doctor or pharmacist before use if you are taking any other drug. Take this product two or more hours before or after other drugs. Laxatives may affect how other drugs work.

Stop use and ask a doctor if

- you have rectal bleeding or fail to have bowel movement after use of a laxative. These could be sings of a serious condition.
- you need to use a stool softener laxative for more than 1 week

PREGNANCY OR BREAST FEEDING

If pregnant or breast-feeding, ask a health professional before use.

Keep out of reach of children. In case of overdose, get medical help or contact a Poison Control Center right away.

Directions

adults and children 12 years and over | take 1 -3 softgels once daily or in divided doses
children 2 to under 12 years of age | 1 softgel once daily
children under 2 years | ask a doctor

OTHER SAFETY INFORMATION

- each softgel contains: sodium 5 mg
- store at room temperature 15°-30°C (59°-86°F) and avoid excessive heat

Inactive ingredients

citric acid, D&C red #33, FD&C blue #1, FD&C red #40, FD&C yellow #6, gelatin, glycerin, polyethylene glycol, propylene glycol, purified water, sorbitol special and white edible ink

Questions or comments ?

Call 516-341-066 8:30 am - 4:30 pm ET, Monday - Friday

TAMPER EVIDENT: DO NOT USE IF IMPRINTED SEAL UNDER CAP IS BROKEN OR MISSING.

*Reliable-1 Laboratories LLC is not affiliated with the owner of the trademark Colace®

Distributed by: Reliable-1 Laboratories LLC Valley Stream, NY 11580 www.reliable1labs.com

PRINCIPLINE DISPLAY PANEL - Bottle Label 100ct

NDC 69618-043-01

Docusate Sodium 100 mg 100 SOFTGELS

STOOL SOFTENER LAXATIVE

PRINCIPLINE DISPLAY PANEL - Bottle Label 1000ct

NDC 69618-043-10

Docusate Sodium 100 mg 1000 SOFTGELS

STOOL SOFTENER LAXATIVE